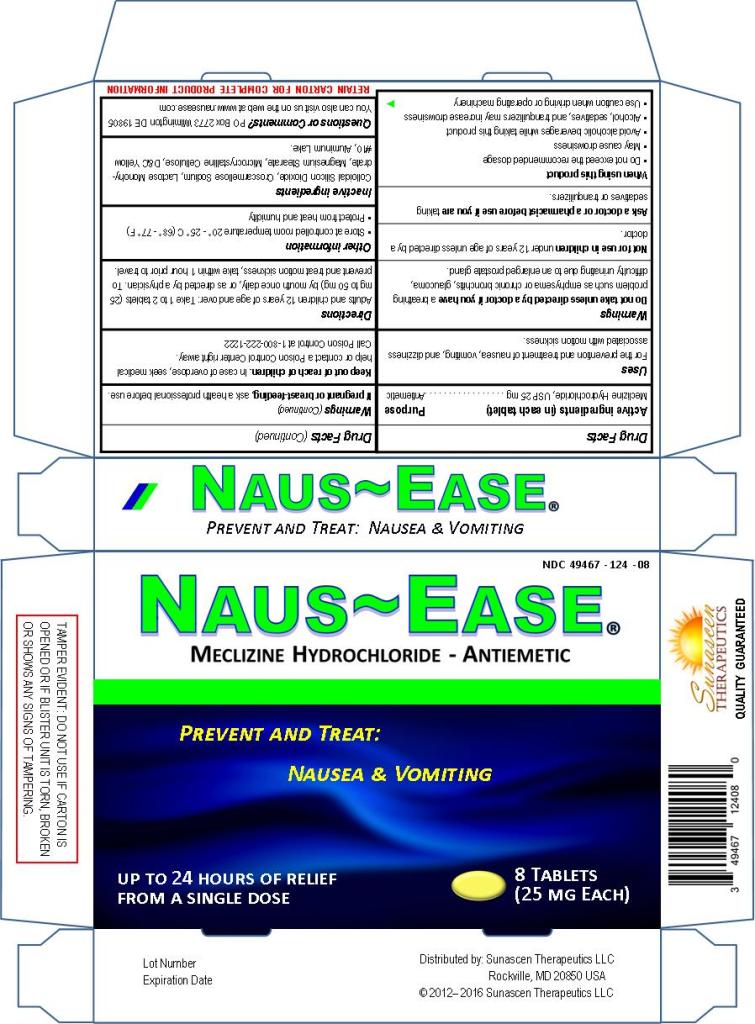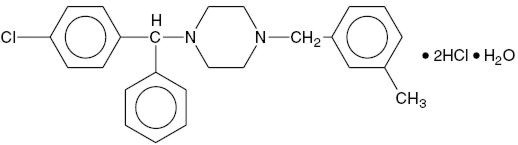 DRUG LABEL: NAUS-EASE
NDC: 49467-124 | Form: TABLET
Manufacturer: Sunascen Therapeutics LLC
Category: otc | Type: HUMAN OTC DRUG LABEL
Date: 20230131

ACTIVE INGREDIENTS: MECLIZINE HYDROCHLORIDE 25 mg/1 1
INACTIVE INGREDIENTS: SILICON DIOXIDE; CROSCARMELLOSE SODIUM; LACTOSE MONOHYDRATE; MAGNESIUM STEARATE; CELLULOSE, MICROCRYSTALLINE; D&C YELLOW NO. 10; ALUMINUM OXIDE

NAUS-EASE® (Meclizine Hydrochloride), USP; Tablet - Product Information

ACTIVE INGREDIENTS

Meclizine Hydrochloride, USP 25 mg

PURPOSE

Antiemetic

DESCRIPTION

Chemically, Meclizine Hydrochloride, USP is 1-(p-Chloro-α-phenylbenzyl)-4-(m-methylbenzyl) piperazine dihydrochloride monohydrate. Meclizine Hydrochloride, USP is an oral antiemetic, which is a white to slightly yellowish crystalline powder having a slight odor and is tasteless. The molecular weight is 481.89 g/mol. It has the following structural formula:

C25H27CIN2·2HCl·H20 M.W. 481.88544 g/mol

CLINICAL PHARMACOLOGY

Meclizine Hydrochloride, USP is an antihistamine that shows marked protective activity against nebulized histamine and lethal doses of intravenously injected histamine in guinea pigs. It has a marked effect in blocking the vasodepressor response to histamine, but only a slight blocking action against acetylcholine. Its activity is relatively weak in inhibiting the spasmogenic action of histamine on isolated guinea pig ileum.

Pharmacokinetics

The available pharmacokinetic information for Meclizine Hydrochloride, USP following oral administration has been summarized from published literature.

Absorption

Meclizine Hydrochloride, USP is absorbed after oral administration with maximum plasma concentrations reaching at a median Tmax value of 3 hours post-dose (range: 1.5 to 6 hours) for the tablet dosage form.

Distribution

Drug distribution characteristics for Meclizine Hydrochloride, USP in humans remains unknown.

Metabolism

The metabolic fate of Meclizine Hydrochloride, USP in humans is unknown. In an in vitro metabolic study using human hepatic microsome and recombinant CYP enzyme, CYP 2D6 was found to be the dominant enzyme for metabolism of Meclizine Hydrochloride, USP.

The genetic polymorphism of CYP2D6 that results in extensive-, poor-, intermediate- and ultrarapid metabolizer phenotypes could contribute to large inter-individual variability in Meclizine Hydrochloride, USP exposure.

Elimination

Meclizine Hydrochloride, USP has a plasma elimination half-life of about 5-6 hours in humans.

INDICATIONS AND USAGE

For Consumers (the general public):
Naus-Ease® (Meclizine Hydrochloride), USP Tablets are used for the prevention and treatment of nausea and vomiting, or dizziness associated with motion sickness.

For Health Professionals:
Based on a review of Meclizine Hydrochloride, USP drug by the National Academy of Sciences – National Research Council and/or other information, FDA has classified the indications of Meclizine Hydrochloride, USP as follows:
1. The prevention and treatment (management) of nausea and vomiting, and dizziness associated with motion sickness.
2. For the treatment of vertigo.

CONTRAINDICATIONS

Meclizine Hydrochloride, USP is contraindicated in individuals who have shown a previous hypersensitivity to it.

WARNINGS

Clinical studies establishing safety and effectiveness in children under 12 years of age have not been done; therefore, usage is not recommended in children under 12 years of age unless directed by a doctor.

Due to its potential anticholinergic action, do not take unless directed by a doctor if you have a breathing problem such as asthma, emphysema, or chronic bronchitis, glaucoma, or difficulty in urination due to enlargement of the prostate gland.

Ask a doctor before use if you are taking sedatives or tranquilizers.

When using this product:
1. Do not exceed the recommended dosage.
2. May cause drowsiness.
3. Patients should avoid alcoholic beverages while taking this drug.
4. Since drowsiness may, on occasion, occur with use of this drug, patients should be warned of this possibility and cautioned against driving a car or operating dangerous machinery. Therefore patients are reminded caution when driving or operating machinery.
5. Alcohol, sedatives and tranquilizers may increase drowsiness.

If pregnant or breast-feeding, ask a health professional before use.

Keep out of reach of children. In case of overdose, seek medical help or contact a Poison Control Center right away.
Call Poison Control at 1-800-222-1222

PRECAUTIONS

Pediatric Use

Clinical studies establishing safety and effectiveness in children under 12 years of age have not been done; therefore, usage is not recommended in children under 12 years of age unless directed by a doctor.

Pregnancy Use

Pregnancy Category B. Reproduction studies in rats have shown cleft palates at 25 to 50 times the human dose. Epidemiological studies in pregnant women, however, do not indicate that Meclizine Hydrochloride, USP increases the risk of abnormalities when administered during pregnancy. Despite the animal findings, it would appear that the possibility of fetal harm is remote. Nevertheless, Meclizine Hydrochloride, USP or any other medication, should be used during pregnancy only if clearly necessary, and after speaking with a health professional.

Nursing Mothers

It is not known whether this drug is excreted in human milk. Because many drugs are excreted in human milk, caution should be exercised when Meclizine Hydrochloride, USP is administered to a nursing woman.

Hepatic Impairment

The effect of hepatic impairment on the pharmacokinetics of meclizine has not been evaluated. As Meclizine Hydrochloride, USP undergoes metabolism, hepatic impairment may result in increased systemic exposure of the drug. Treatment with Meclizine Hydrochloride, USP should be administered with caution in patients with hepatic impairment.

Renal Impairment

The effect of renal impairment on the pharmacokinetics of Meclizine Hydrochloride, USP has not been evaluated. Due to a potential for drug/metabolite accumulation, Meclizine Hydrochloride, USP should be administered with caution in patients with renal impairment and in the elderly as renal function generally declines with age.

Drug Interactions

There may be increased CNS depression when Meclizine Hydrochloride, USP is administered concurrently with other CNS depressants, including alcohol, tranquilizers and sedatives. (see WARNINGS)

Based on in vitro evaluation, Meclizine Hydrochloride, USP is metabolized by CYP2D6. Therefore there is a possibility for a drug interaction between Meclizine Hydrochloride, USP and CYP2D6 inhibitors.

Keep out of reach of children. In case of an overdose, seek medical help or contact a Poison Control Center immediately.
Call Poison Control at 1-800-222-1222.

ADVERSE REACTIONS

Anaphylactoid reaction, drowsiness, dry mouth, headache, fatigue, vomiting and, on rare occasions, blurred vision have been reported.

DOSAGE AND ADMINISTRATION (DIRECTIONS)

Adults and children 12 years of age and over: Take 1 to 2 Naus-Ease® (Meclizine Hydrochloride), USP Tablets (25 mg to 50 mg) by mouth once daily, or as directed by a physician.

The initial dose of 25 mg to 50 mg of Naus-Ease® (Meclizine Hydrochloride), USP Tablets should be taken one hour prior to travel for the prevention and treatment of motion sickness. Thereafter, the dose may be repeated every 24 hours for the duration of the journey.

INACTIVE INGREDIENTS

Each tablet contains the following inactive ingredients: Colloidal Silicon Dioxide, Croscarmellose Sodium, Lactose Monohydrate, Magnesium Stearate, Microcrystalline Cellulose, D&C Yellow #10, Aluminum Lake (15-20%).

OTHER USEFUL INFORMATION

Store at controlled room temperature 20-25°C (68-77°F).

Protect from heat and humidity.

Use by expiration date on package.

HOW SUPPLIED

Naus-Ease® (Meclizine Hydrochloride), USP Tablets are available in 25mg strengths, and is available in 8 and 16 count package sizes.

25 mg tablets; Yellow; Oval shaped; Scored; "TL121" imprinted on each tablet

Naus-Ease® (Meclizine Hydrochloride), USP; 8 Tablets: NDC 49467-124-08
Naus-Ease® (Meclizine Hydrochloride), USP; 16 Tablets: NDC 49467-124-16

Distributed by:
Sunascen Therapeutics LLC
Rockville, MD 20850 USA

QUESTIONS OR COMMENTS?

Sunascen Therapeutics LLC
PO Box 2773
Wilmington DE 19805

More information is available on the web at www.nausease.com

PRINCIPAL DISPLAY PANEL

Naus-Ease® (Meclizine Hydrochloride), USP; Tablets 25 mg Each
Antiemetic – Prevent and Treat: Nausea and Vomiting

TAMPER EVIDENT: DO NOT USE IF CARTON IS OPENED OR IF BLISTER UNIT IS TORN, BROKEN OR SHOWS ANY SIGNS OF TAMPERING.